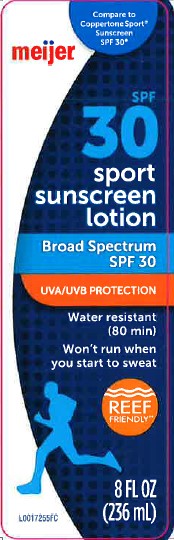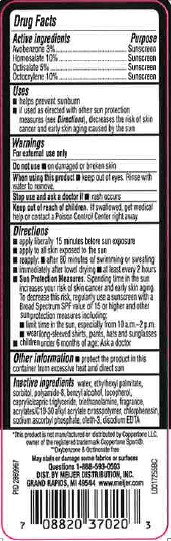 DRUG LABEL: Sunscreen
NDC: 41250-714 | Form: LOTION
Manufacturer: Meijer, Inc.
Category: otc | Type: HUMAN OTC DRUG LABEL
Date: 20260219

ACTIVE INGREDIENTS: AVOBENZONE 30.3 mg/1 mL; HOMOSALATE 101 mg/1 mL; OCTISALATE 50.5 mg/1 mL; OCTOCRYLENE 101 mg/1 mL
INACTIVE INGREDIENTS: WATER; ETHYLHEXYL PALMITATE; SORBITOL; POLYAMIDE-8 (4500 MW); BENZYL ALCOHOL; TOCOPHEROL; MEDIUM-CHAIN TRIGLYCERIDES; TROLAMINE; CARBOMER INTERPOLYMER TYPE A (ALLYL SUCROSE CROSSLINKED); CHLORPHENESIN; SODIUM ASCORBYL PHOSPHATE; OLETH-3; EDETATE DISODIUM ANHYDROUS

Meijer 714.000/714AA
Sport Sunscreen Lotion SPF 30

Active Ingredients

Avobenzone 3%

Homosalate 10%

Octisalate 5%

Octocrylene 10%

Purpose

Sunscreen

Uses

- helps prevent sunburn
- if used as directed with other sun protections measures (see Directions), decreases the rist of skin cancer and early skin aging caused by the sun

Warnings

For external use only

Do not use

- on damaged or broken skin

When using this product

- keep out of eyes. Rinse with water to remove

Stop use and ask a doctor if

- rash occurs

Keep out of reach of children

if swallowed, get medical help or contact a Poison Control Center right away

Directions

- apply liberally 15 minutes before sun exposure
- reapply:
- after 80 minutes of swimming or sweating
- immediately after towel drying
- at least every 2 hours
- Sun Protection Measures. Spending time in the sun increases your risk of skin cancer and early skin aging. To decrease this risk, regularly use a sunscreen with a Broad Spectrum SPF value of 15 or higher and other sun protection measures including:
- limit time in the sun, especiallyu from 10 a.m. - 2 p.m.
- wear long-sleeved shirts, pants, hats and sunglasses
- children under 6 months of age: Ask a doctor

Other Information

- Protect the product from excessive heat and direct sun

Inactive ingredients

water, ethylhexyl palmitate, sorbitol, polyamide-8, benzyl alcohol, tocopherol, caprylic/capric triglyceride, triethanolamine, fragrance, acrylates/C10-30 alkyl acrylate crosspolymer, chlorphenesin, sodium ascorbyl phosphate, oleth-3, disodium EDTA

disclaimer

*This product is not manufactured or distributed by Coppertone LLC, owner of the registered trademark Coppertone Sport

**Oxybenzone & Octinoxate free

May stain or damage some fabrics or surfaces

Adverse reactions section

Questions 1-888-593-0593

DIST. BY MEIJER DISTRIBUTION, INC.

GRAND RAPIDS, MI 49544 www,meijer.com

PRINCIPAL DISPLAY PANEL

Compare to

Coppertone Sport

Sunscreen

SPF 30

meijer

SPF

30

sport

sunscreen

lotion

Broad Spectrum SPF 30

UVA/UVB PROTECTION

Water Resistant

(80 min)

Won't run when you start to sweat

REEF

FRIENDLY**

8 FL OZ

(236 mL)